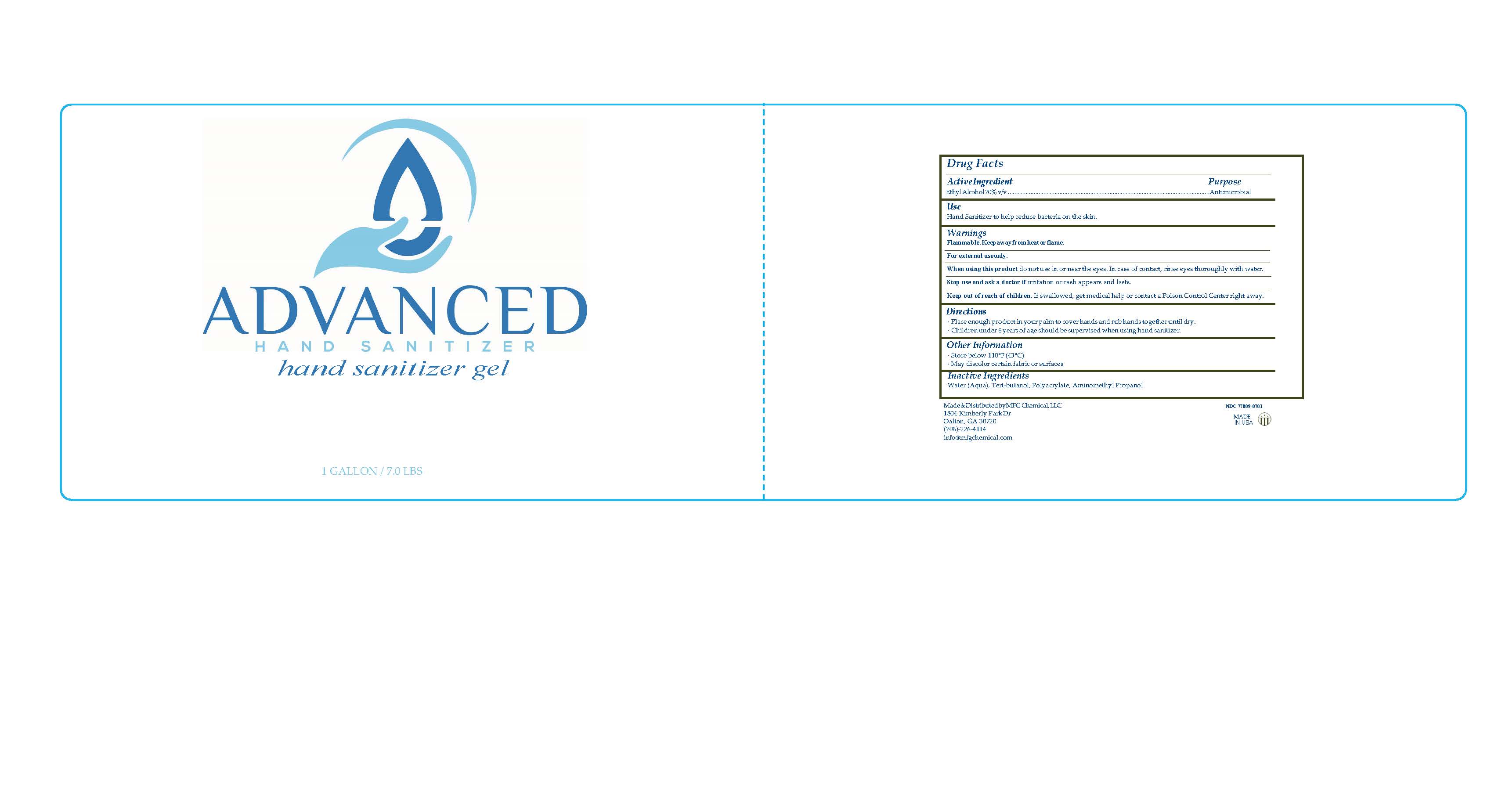 DRUG LABEL: Advanced
NDC: 77809-070 | Form: GEL
Manufacturer: MFG Chemical, LLC.
Category: otc | Type: HUMAN OTC DRUG LABEL
Date: 20200917

ACTIVE INGREDIENTS: ALCOHOL 70 mL/100 mL
INACTIVE INGREDIENTS: WATER 29.23 mL/100 mL; TERT-BUTYL ALCOHOL 0.125 mL/100 mL; POLYACRYLIC ACID (800000 MW) 0.4 mL/100 mL; AMINOMETHYLPROPANOL 0.25 mL/100 mL

Active Ingredient Purpose

Ethyl Alcohol 80% v/v............................................................................................................................................................. Antimicrobial

INACTIVE INGREDIENT

Hand Sanitizer to help reduce bacteria on the skin.

WARNINGS

Flammable. Keep away from heat or flame.

For external use only.

When using this product do not use in or near the eyes. In case of contact, rinse eyes thoroughly with water.

Stop use and ask a doctor if irritation or rash appears and lasts.

Keep out of reach of children. If swallowed, get medical help or contact a Poison Control Center right away.

DOSAGE AND ADMINISTRATION

- Place enough product in your palm to cover hands and rub hands together until dry.
- Children under 6 years of age should be supervised when using hand sanitizer.

OTHER SAFETY INFORMATION

Store below 110oF (43oC)

May discolor certain fabrics or surfaces

INACTIVE INGREDIENT

Water (Aqua), Tert-butanol, Polyacrylate, Aminomethyl Propanol

INDICATIONS AND USAGE

For external use only

Keep out of reach of children. If swallowed, get medical help or contact a Poison Control Center right away.

PURPOSE

Hand Sanitizer to help reduce bacteria on the skin.